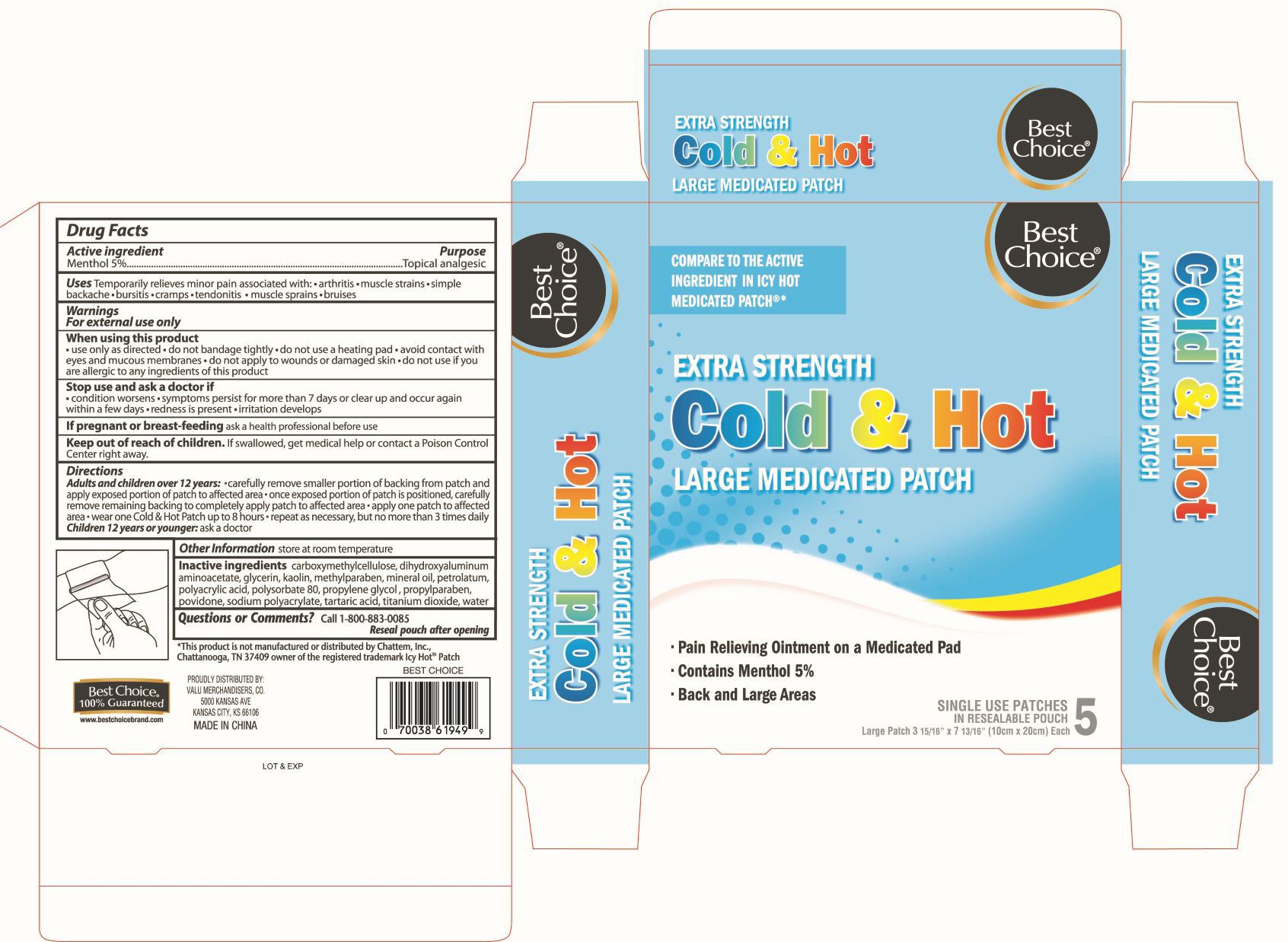 DRUG LABEL: Cold and Hot Medicated Pain Relief Large
NDC: 63941-948 | Form: PATCH
Manufacturer: Valu Merchandisers Company, Inc.
Category: otc | Type: HUMAN OTC DRUG LABEL
Date: 20220706

ACTIVE INGREDIENTS: MENTHOL 550 mg/1 1
INACTIVE INGREDIENTS: PETROLATUM; SODIUM POLYACRYLATE (8000 MW); POVIDONE; DIHYDROXYALUMINUM AMINOACETATE; GLYCERIN; KAOLIN; METHYLPARABEN; CARBOXYMETHYLCELLULOSE; POLYSORBATE 80; WATER; POLYETHYLENE GLYCOL 400; POLYACRYLIC ACID (8000 MW); TARTARIC ACID; TITANIUM DIOXIDE; PROPYLPARABEN; MINERAL OIL

Best Choice Cold & Hot Large Medicated Patch

Active Ingredient

Menthol 5%

Purpose

Topical analgesic

Uses

Temporarily relieves minor pain associated with:

- arthritis
- muscle strains
- simple backache
- bursitis
- cramps
- tendonitis
- muscle sprains
- bruises

Warnings

For external use only

When using this product

- use only as directed
- do not bandage tightly or use with heating pad
- avoid contact with eyes and mucous membranes
- do not apply to wounds or damaged skin
- do not use if you are allergic to any ingredients of this product

Stop use and ask a doctor if

- condition worsens
- symptoms persist for more than 7 days or clear up and occur again within a few days
- redness is present
- irritation develops

If pregnant or breast-feeding,

ask a health professional before use.

Keep out of reach of children.

If swallowed, get medical help or contact a Poison Control Center immediately.

Directions

Adults and children over 12 years:

- carefully remove backing from patch
- apply one patch to affected area
- repeat as necessary, but no more than 4 times daily

Children under 12 years of age: Ask a doctor

Inactive ingredients

carboxymethylcellulose, dihydroxyaluminum aminoacetate, glycerin, kaolin, methylparaben, mineral oil, petrolatum, polyacrylic acid, polysorbate 80, propylene glycol, povidone, propylparaben, sodium polyacrylate, tartaric acid, titanium dioxide, water

Questions or Comments?

call 1-800-883-0085

Reseal pouch after opening

package label

Best Choice Cold and Hot Large Medicated Patch